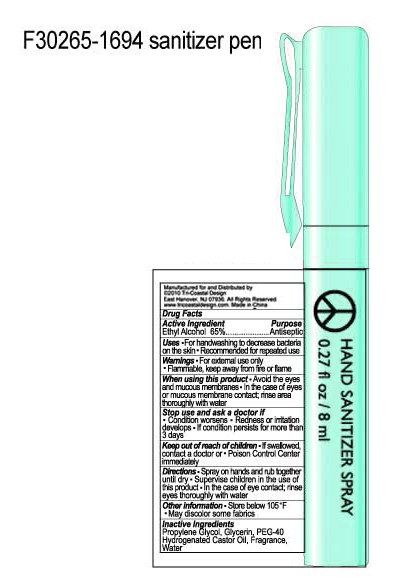 DRUG LABEL: Waterless Anti-Bacterial Hand Cleanser
NDC: 49852-001 | Form: LIQUID
Manufacturer: Tri-Coastal Design Company Inc. 
Category: otc | Type: HUMAN OTC DRUG LABEL
Date: 20091230

ACTIVE INGREDIENTS: ALCOHOL 65 mL/100 mL
INACTIVE INGREDIENTS: PROPYLENE GLYCOL; GLYCERIN; POLYOXYL 40 HYDROGENATED CASTOR OIL; WATER

Drug Facts

Active Ingredient
Alcohol 65%

Purpose
Antiseptic

Use

- For handwashing to decrease bacteria on the skin
- Recommended for repeated use

Warnings

- For external use only
- Flammable, keep away from fire and flame

When using this product

- Avoid the eyes and mucous membranes
- In the case of eyes or mucous membrane contact, rinse area thoroughly with water

Stop use and ask a doctor if

- Condition worsens
- Redness or irritation develops
- If condition persists for more than 3 days

Keep out of reach of children If swallowed contact a doctor or Poison Control Center immediately

Directions

- Spray on hands and rub together until dry
- Supervise children in the use of this product
- In the case of eye contact, rinse eyes thoroughly with water

Other Information

- Store below 105 F
- May discolor some fabrics

INACTIVE INGREDIENT

Inactive ingredients Propylene Glycol, PEG-40 Hydrogenated Castor Oil, Fragrance, Water

Package Label